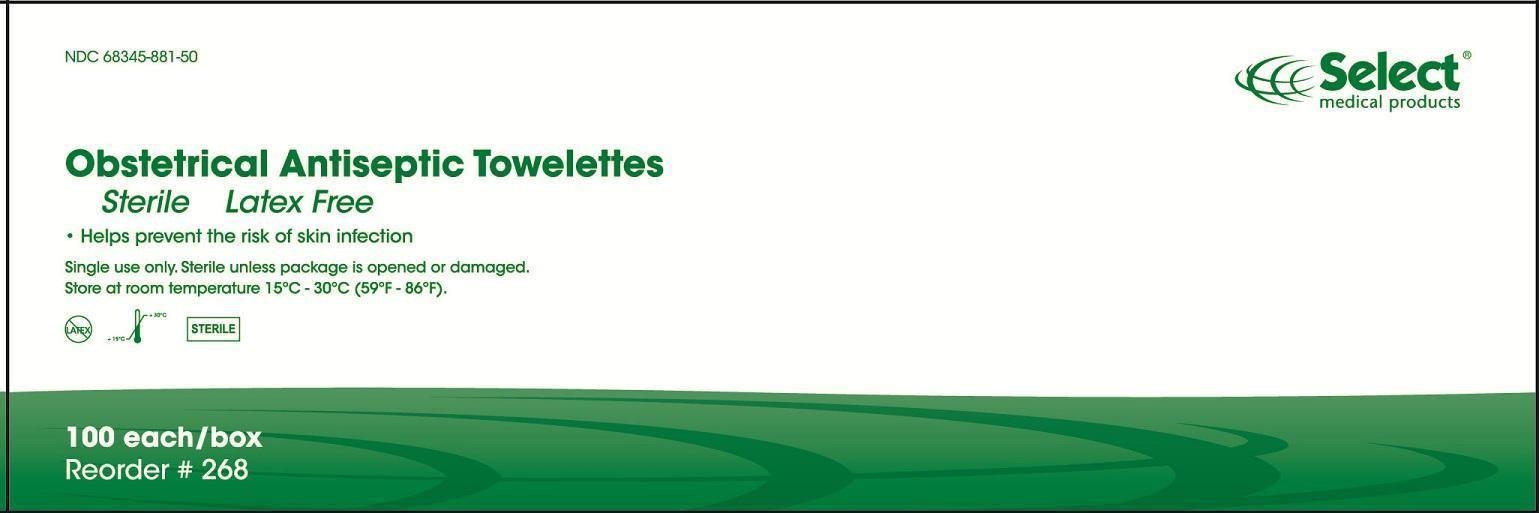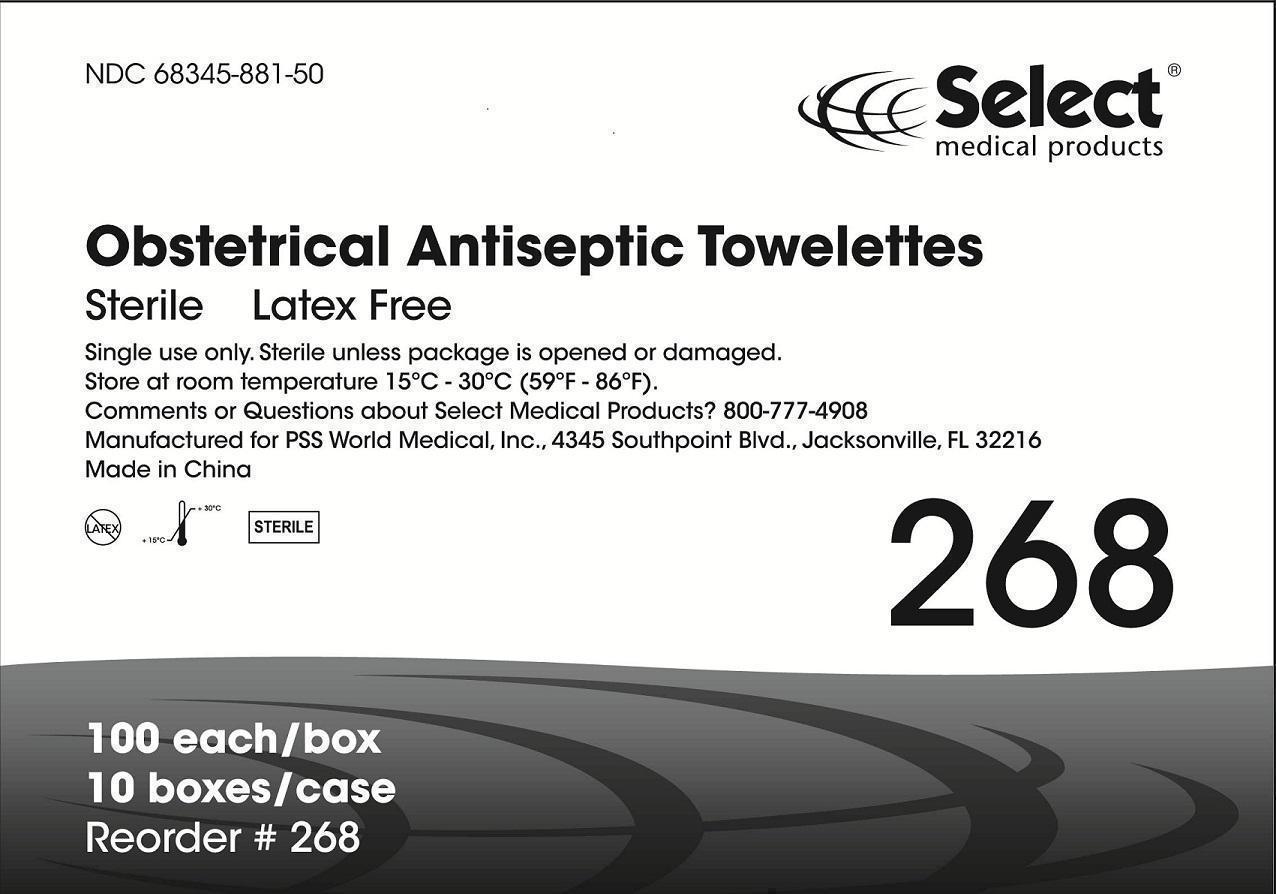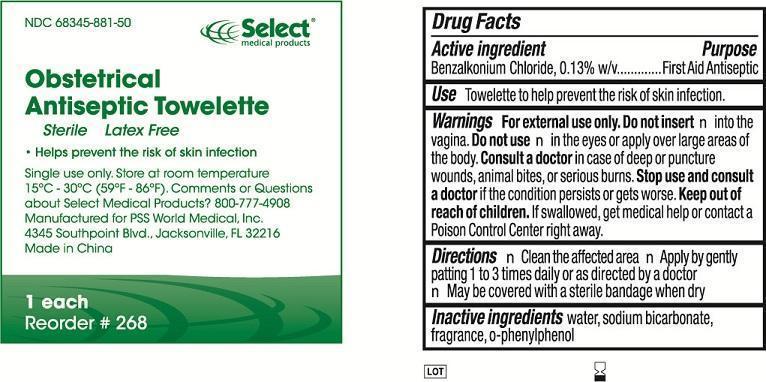 DRUG LABEL: Obstetrical Antiseptic Towelette
NDC: 68345-881 | Form: LIQUID
Manufacturer: PSS World Medical, Inc.
Category: otc | Type: HUMAN OTC DRUG LABEL
Date: 20130627

ACTIVE INGREDIENTS: BENZALKONIUM CHLORIDE 0.13 g/100 g
INACTIVE INGREDIENTS: WATER; SODIUM BICARBONATE; O-PHENYLPHENOL

Obstetrical Antiseptic Towelette (BENZALKONIUM CHLORIDE) Liquid
[PSS World Medical]

Active ingredient

Benzalkonium Chloride, 0.13% w/v

Purpose

First Aid Antiseptic

INDICATIONS AND USAGE

Use Towelette to help prevent the risk of skin infection.

Warnings

For external use only.

Do not insert into the vagina.

Do not use

- in the eyes or apply over large areas of the body.

STOP USE

Consult a doctor in case of deep or puncture wounds, animal bites, or serious burns.

Stop use and consult a doctor if the condition persists or gets worse.

Keep out of reach of children. If swallowed, get medical help or contact a Poison Control Center right away.

Directions

- Clean the affected area
- Apply by gently patting 1 to 3 times daily or as directed by a doctor
- May be covered with a sterile bandage when dry

Inactive ingredient: water, sodium bicarbonate, fragrance, o-phenylphenol

Questions or Comments about Select Medical Products? 800-777-4908

DESCRIPTION

Manufactured for PSS World Medical, Inc.

4345 Southpoint Blvd., Jacksonville, FL 32216

Made in China

Package Label

Reorder #268

NDC 68345-881-50

268_Each

268_Box

268_Case